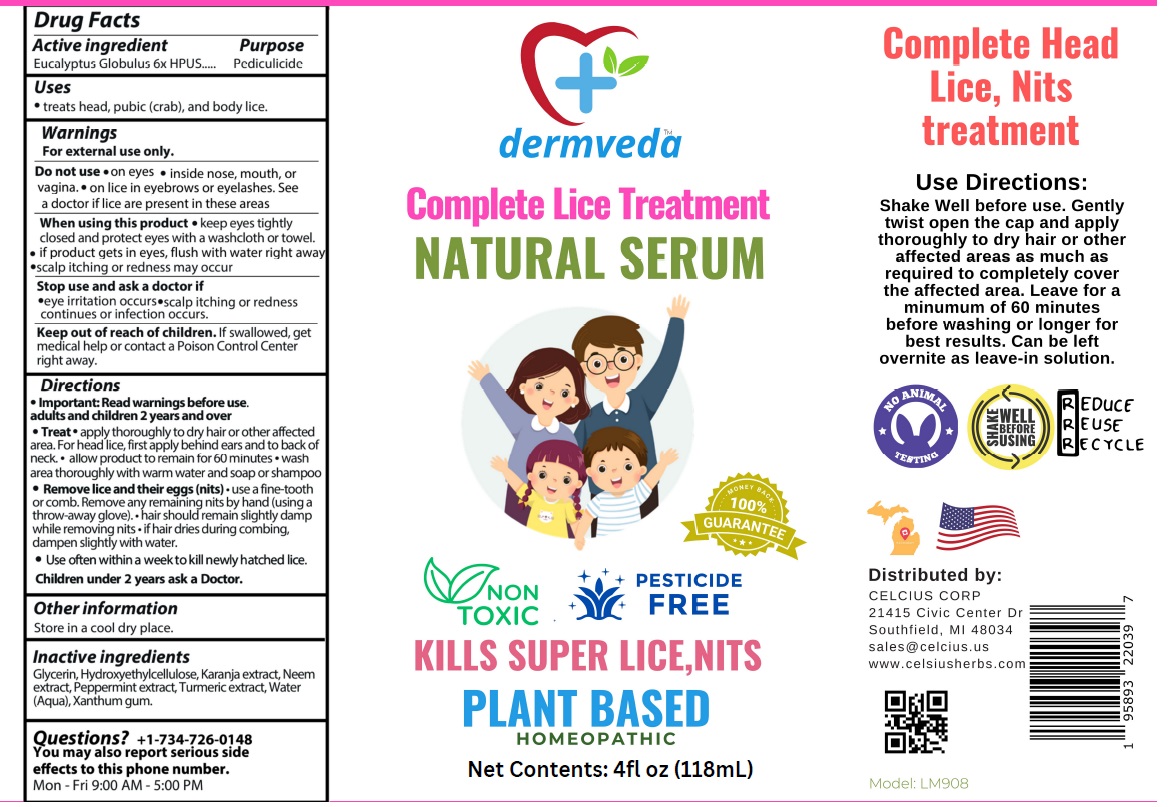 DRUG LABEL: dermveda Complete Lice Treatment NATURAL SERUM
NDC: 83819-030 | Form: LIQUID
Manufacturer: Celcius Corp.
Category: homeopathic | Type: HUMAN OTC DRUG LABEL
Date: 20260206

ACTIVE INGREDIENTS: EUCALYPTUS GLOBULUS LEAF 6 [hp_X]/118 mL
INACTIVE INGREDIENTS: GLYCERIN; HYDROXYETHYL CELLULOSE, UNSPECIFIED; PONGAMIA PINNATA WHOLE; AZADIRACHTA INDICA FLOWER; PEPPERMINT; TURMERIC; WATER; XANTHAN GUM

dermveda™ Complete Lice Treatment NATURAL SERUM

Active ingredient

Eucalyptus Globulus 6x HPUS

Purpose

Pediculicide

Uses

• treats head, pubic (crab), and body lice.

Warnings

For external use only.

Do not use • on eyes • inside nose, mouth or vagina. • on lice in eyebrows or eyelashes. See a doctor if lice are present in these areas

When using this product • keep eyes tightly closed and protect eyes with a washcloth or towel. • if product gets in eyes, flush with water right away • scalp itching or redness may occur

Stop use and ask a doctor if
• eye irritation occurs • scalp itching or redness continues or infection occurs.

Keep out of reach of children. If swallowed, get medical help or contact a Poison Control Center right away.

Directions

• Important: Read warnings before use.
adults and children 2 years and over

• Treat • apply thoroughly to dry hair or other affected area. For head lice, first apply behind ears and to back of neck. • allow product to remain for 60 minutes. • wash area thoroughly with warm water and soap or shampoo

• Remove lice and their eggs (nits) • use a fine-tooth or comb. • Remove any remaining nits by hand (using a throw-away glove). • hair should remain slightly damp while removing nits. If hair dries during combing, dampen slightly with water.

• Use often within a week to kill newly hatched lice.

Children under 2 years ask a Doctor.

Other information

Store in a cool dry place.

Inactive ingredients

Glycerin, Hydroxyethylcellulose, Karanja extract, Neem extract, Peppermint extract, Turmeric extract, Water (Aqua), Xanthan gum.

Questions?

+1-734-726-0148
You may also report serious side effects to this phone number.
Mon - Fri 9:00 AM -5:00 PM

MONEY BACK 100% GUARANTEE

NON TOXIC

PESTICIDE FREE

KILLS SUPER LICE, NITS

PLANT BASED

HOMEOPATHIC

Use Directions:
Shake Well before use. Gently twist open the cap and apply thoroughly to dry hair or other affected areas as much as required to completely cover the affected area. Leave for a minimum of 60 minutes before washing or longer for best results. Can be left over nite as leave-in solution.

NO ANIMAL TESTING

REDUCE
REUSE
RECYCLE

Distributed by:
CELCIUS CORP
21415 Civic Center Dr
Southfield, MI 48034
sales@celcius.us
www.celsiusherbs.com